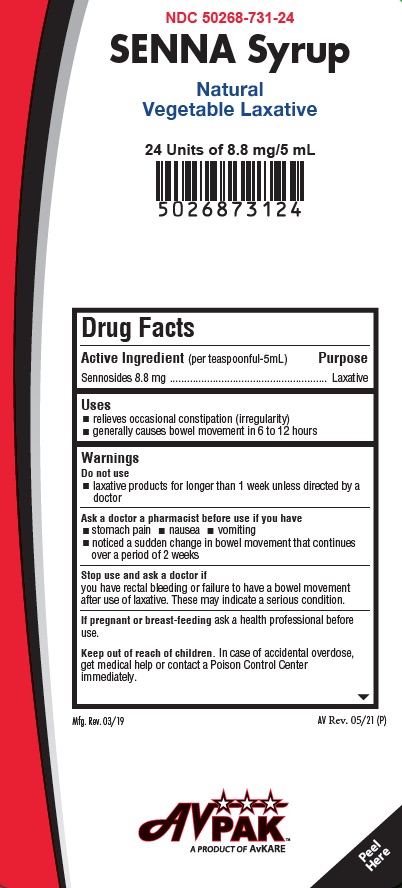 DRUG LABEL: Senna Syrup
NDC: 50268-731 | Form: LIQUID
Manufacturer: AVPAK
Category: otc | Type: HUMAN OTC DRUG LABEL
Date: 20260109

ACTIVE INGREDIENTS: SENNOSIDES 8.8 mg/5 mL
INACTIVE INGREDIENTS: METHYLPARABEN; PROPYLENE GLYCOL; PROPYLPARABEN; WATER; SUCRALOSE

Senna Syrup

Drug Facts

Active Ingredient (in each 5 mL = 1 teaspoonful)
Sennosides 8.8 mg

Purpose
Laxative

INDICATIONS AND USAGE

Use: • relieves occasional constipation (irregularity), generally causes bowel movement in 6-12 hours.

WARNINGS

WARNINGS: Do not use • laxative products for a period longer than 1 week unless directed by a doctor

Ask a doctor before use if you have • stomach pain • nausea • vomiting • noticed a sudden change in bowel movement that continues over a period of 2 weeks

Stop use and ask a doctor if you have • rectal bleeding • no bowel movement after use of laxative

These could be signs of a serious condition.

PREGNANCY OR BREAST FEEDING

If pregnant or breast feeding, ask a health care professional before use.

KEEP OUT OF REACH OF CHILDREN

Keep this and all drugs out of reach of children. In case of overdose, get medical help or contact a Poison Control Center immediately. In case of eye contact, flush with water.

Directions:
- Shake well before use
- Do not exceed recommended dose
Age | Starting Dose | Maximum Dosage
Adults and children 12 years of age and over | 2 to 3 teaspoonfuls (10 mL to 15 mL) once a day preferably at bedtime; increase as needed or as recommended by a doctor | 3 teaspoonfuls (15 mL) in the morning and 3 teaspoonfuls (15 mL) at bedtime
Children under 12 years of age | Ask a doctor | Ask a doctor
1 teaspoonful = 5 mL

Other information: Store at room temperature 15°C to 25°C (59°F to 77°F). Excursions between 26°C to 30°C (78°F to 86°F) are allowed. Protect from excessive heat. For more info call 1- 800-447-1006.

INACTIVE INGREDIENT

Inactive ingredients: Artificial and natural chocolate flavor, methylparaben, propylparaben, propylene glycol, sucrose and purified water.